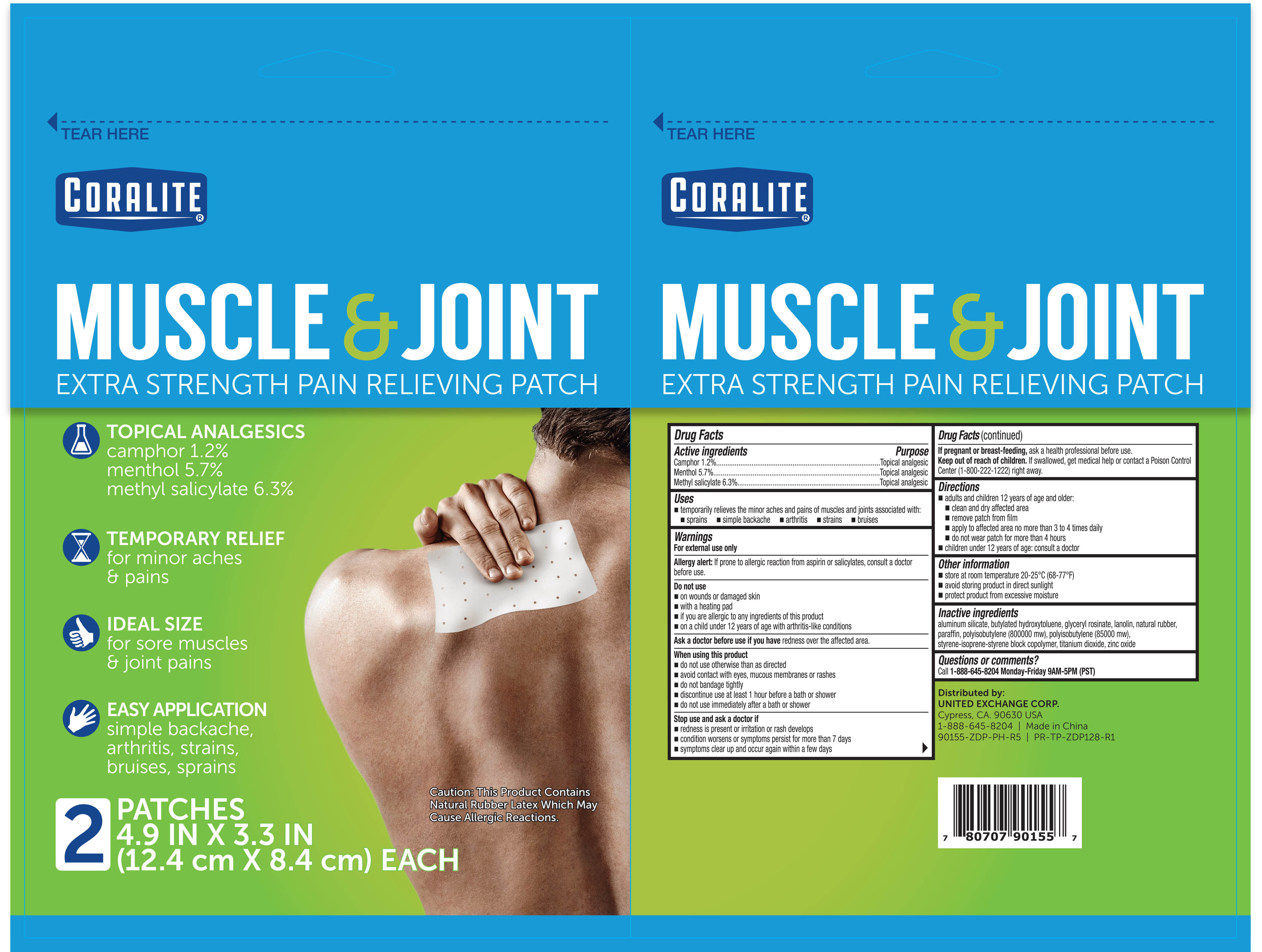 DRUG LABEL: Coralite Muscle and Joint Pain Relief
NDC: 65923-148 | Form: PATCH
Manufacturer: United Exchange Corporation
Category: otc | Type: HUMAN OTC DRUG LABEL
Date: 20251024

ACTIVE INGREDIENTS: CAMPHOR (SYNTHETIC) 12 mg/1 g; MENTHOL 57 mg/1 g; METHYL SALICYLATE 63 mg/1 g
INACTIVE INGREDIENTS: ALUMINUM SILICATE; BUTYLATED HYDROXYTOLUENE; GLYCERYL ROSINATE; LANOLIN; NATURAL LATEX RUBBER; PARAFFIN; POLYISOBUTYLENE (800000 MW); POLYISOBUTYLENE (85000 MW); STYRENE/ISOPRENE/STYRENE BLOCK COPOLYMER (STYRENE/ISOPRENE 15/85); TITANIUM DIOXIDE; ZINC OXIDE

Coralite Muscle & Joint Pain Relief patch 2ct (90155)

Active Ingredients Purposes

Camphor 1.2%...................Topical analgesic

Menthol 5.7%.....................Topical analgesic

Methyl salicylate 6.3%.......Topical analgesic

Uses

- temporarily relieves the minor aches and pains of muscles and joints associated with:
- sprains
- simple backache
- arthritis
- strains
- bruises

WARNINGS

For external use only

Allergy alert: If prone to allergic reaction from aspirin or salicylates, consult a doctor before use.

Do not use

- on wounds or damaged skin
- with a heating pad
- if you are allergic to any ingredients of this product
- on a child under 12 years of age with arthritis-like conditions

Ask a doctor before use if you have redness over the affected area.

When using this product

- do not use otherwise than as directed
- avoid contact with eyes, mucous membranes or rashes
- do not bandage tightly
- discontinue use at least 1 hour before a bath or shower
- do not use immediately after a bath or shower

Stop use and ask a doctor if

- redness is present or irritation or rash develops
- conditioin worsens or symptoms persist for more than 7 days
- symptoms clear up and occur again within a few days

PREGNANCY OR BREAST FEEDING

If pregnant or breast-feeding, ask a health professional before use.

Keep out of reach of children. If swallowed, get medical help or contact a Poison Control Center (1-800-222-1222) right away.

Directions

- adults and children 12 years of age and older:
- clean and dry affected area
- remove patch from film
- apply to affected area no more than 3 to 4 times daily
- do not wear patch for more than 4 hours
- children under 12 years of age: consult a doctor

STORAGE AND HANDLING

- store at room temperature 20-25°C (68-77ºF)
- avoid storing product in direct sunlight
- protect product from excessive moisture

Inactive ingredients

aluminum silicate, butylated hydroxytoluene, glyceryl rosinate, lanolin, natural rubber, paraffin, polyisobutylene (800000 mw), polyisobutylene (85000 mw), styrene-isoprene-styrene block copolymer, titanium dioxide, zinc oxide

QUESTIONS

Call 1-800-814-8028 Monday-Friday 9AM-5PM (PST)

DOSAGE AND ADMINISTRATION

Distributed By:

UNITED EXCHANGE CORP.

Cypress, CA. 90630 USA

Made in China